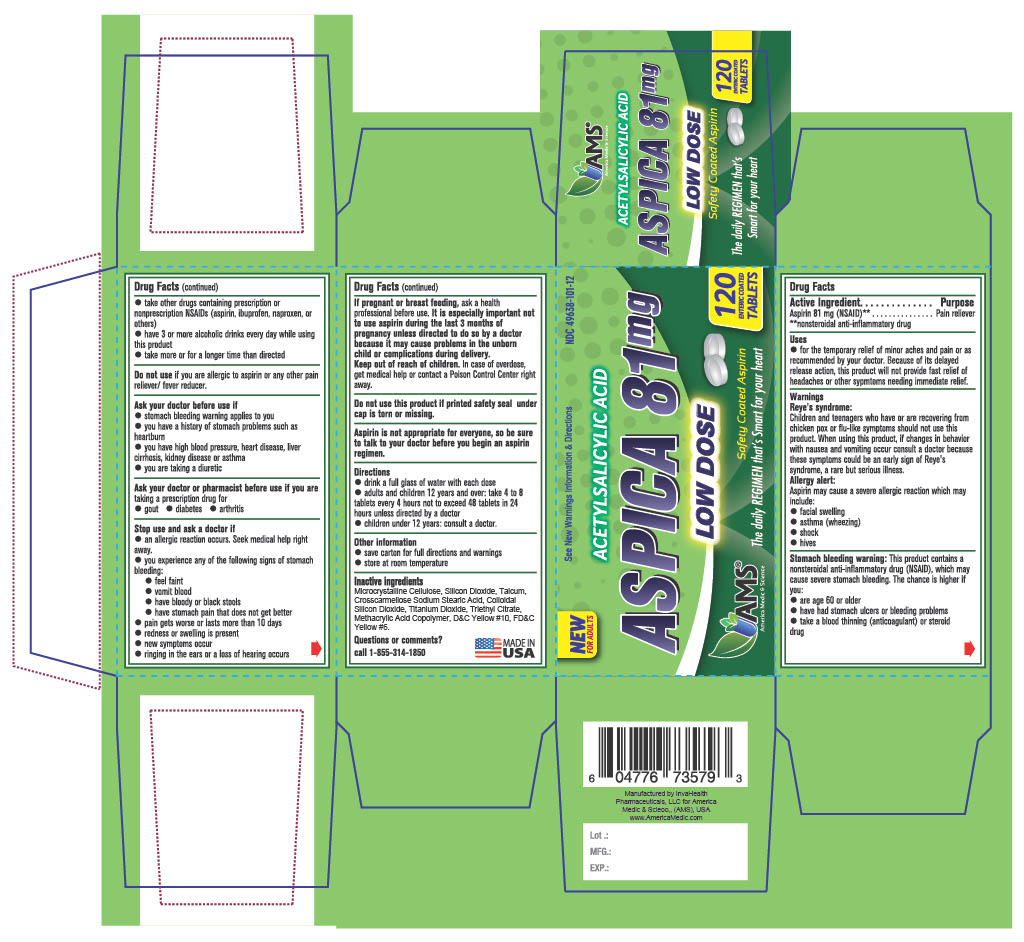 DRUG LABEL: Aspica (Aspirin)
NDC: 49638-101 | Form: TABLET, DELAYED RELEASE
Manufacturer: America Medic & Science, LLC
Category: otc | Type: HUMAN OTC DRUG LABEL
Date: 20240116

ACTIVE INGREDIENTS: ASPIRIN 81 mg/1 1
INACTIVE INGREDIENTS: TRIETHYL CITRATE; TALC; CROSCARMELLOSE SODIUM; TITANIUM DIOXIDE; FD&C YELLOW NO. 6; CELLULOSE, MICROCRYSTALLINE; METHACRYLIC ACID - METHYL METHACRYLATE COPOLYMER (1:1); D&C YELLOW NO. 10; STEARIC ACID; SILICON DIOXIDE

Aspirin Delayed-Release Tablets, USP 81 MG Low Dose Safety Coated Aspirin

Drug Facts

Active ingredient

Aspirin 81 mg (NSAID)**

**nonsteroidal anti-inflammatory drug

Uses

- for the temporary relief of minor aches and pains or as recommended by your doctor. Because of its delayed release action, this product will not provide fast relief of headaches or other symptoms needing immediate relief.

Warnings

Reye's syndrome: Children and teenagers who have or are recovering from chicken pox or flu-like symptoms should not use this product. When using this product, if changes in behavior with nausea and vomiting occur consult a doctor because these symptoms could be an early sign of Reye's syndrome, a rare but serious illness.

Allergy alert: Aspirin may cause a severe allergic reaction which may include:

- facial swelling
- asthma (wheezing)
- shock
- hives

WARNINGS

Stomach bleeding warning: This product contains a nonsteroidal anti-inflammatory drug (NSAID), which may cause severe stomach bleeding. The chance is higher if you:

- are age 60 or older
- have had stomach ulcers or bleeding problems
- take a blood thinning (anticoagulant) or steroid problems
- take other drugs containing prescription or nonprescription NSAIDs (aspirin, ibuprofen, naproxen, or others)
- have 3 or more alcoholic drinks every day while using this product
- take more or for a longer time than directed

Do not use if you are allergic to aspirin or any other pain reliever/ fever reducer.

Ask your doctor before use

- stomach bleeding warning applies to you
- you have a history of stomach problems such as heartburn
- you have high blood pressure, heart disease, liver cirrhosis, kidney disease or asthma
- you are taking a diuretic

ASK DOCTOR/PHARMACIST

Ask your doctor or pharmacist before use if you are taking a prescription drug for

- gout
- diabetes
- arthritis

Stop use and ask doctor if

an allergic reaction occurs. Seek medical help right away.

you experience any of the following signs of stomach bleeding:

- feel faint
- vomit blood
- have bloody or black stools
- have stomach pain that does not get better
- pain gets worse or lasts more than 10 days
- redness or swelling is present
- new symptoms occur
- ringing in the ears or a loss of hearing occurs

PREGNANCY OR BREAST FEEDING

If pregnant or breast feeding, ask a health professional before use. It is especially important not to use aspirin during the last 3 months of pregnancy unless directed to do so by a doctor because it may cause problems in the unborn child or complications during delivery.

Keep out of reach of children. In case of overdose, get medical help or contact a Poison Control Center right away.

Do not use this product if printed safety seal under cap is torn or missing.

ASK DOCTOR

Aspirin is not appropriate for everyone, so be sure to talk to your doctor before you begin an aspirin regimen.

DOSAGE AND ADMINISTRATION

- drink a full glass of water with each dose
- adults and children 12 years and over: take 4 to 8 tablets every 4 hours not to exceed 48 tablets in 24 hours unless directed by a doctor
- children under 12 years: consult a doctor

Other information

- save carton for full directions and warnings
- store at room temperature

Inactive ingredients

Colloidal silicon dioxide, Croscarmellose sodium, Colloidal silicon dioxide, D&C Yellow #10 al lake, FD&C Yellow #6 al lake, methacrylic acid copolymer, microcrystalline cellulose, stearic acid, talc, titanium dioxide, triethyl citrate

Questions or comments?

call 1-855-314-1850